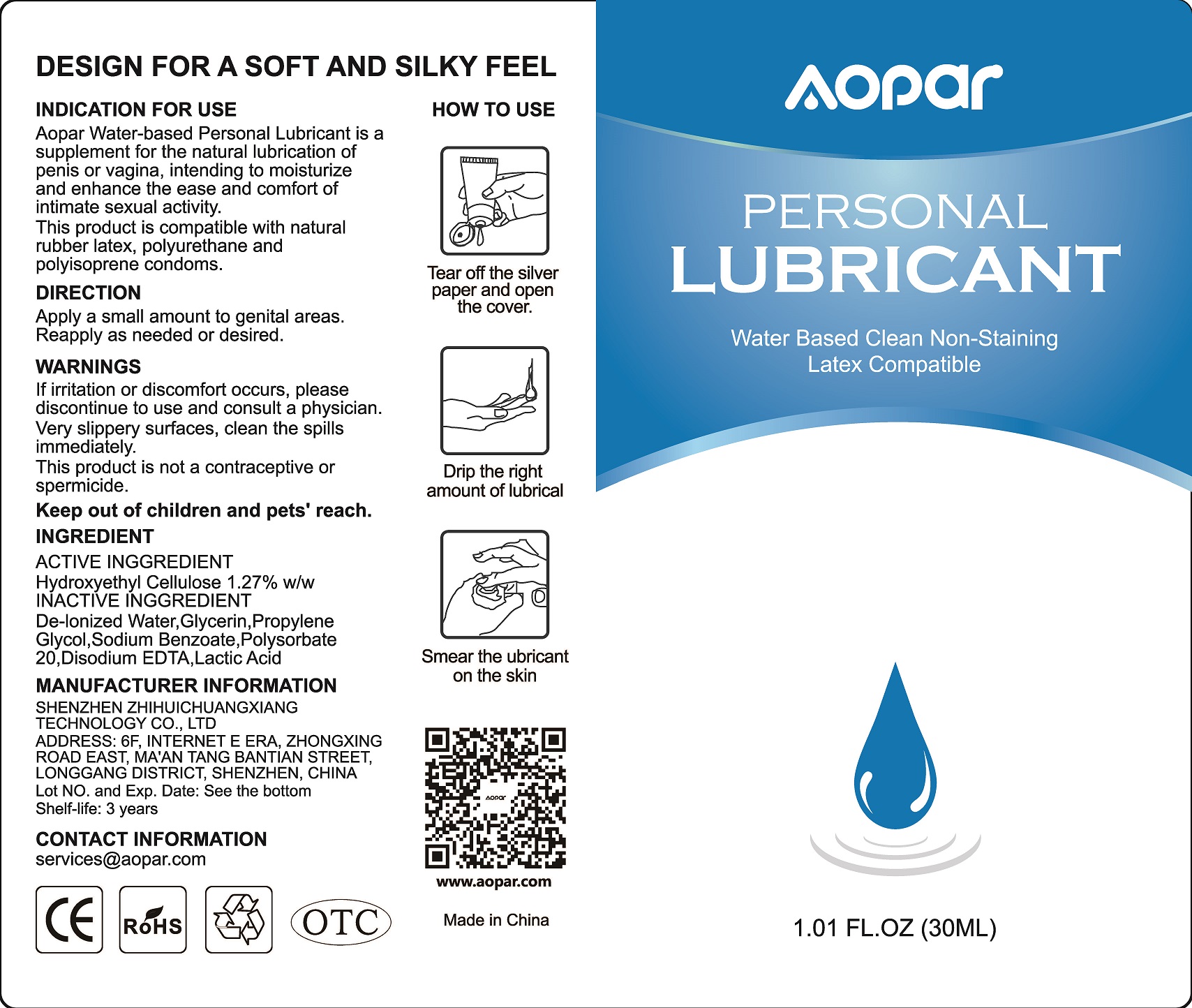 DRUG LABEL: AOPAR Water Based Personal Lubricant
NDC: 73000-226 | Form: LOTION
Manufacturer: Shenzhen ZhiHuiChuangXiang Technology Co., Ltd
Category: otc | Type: HUMAN OTC DRUG LABEL
Date: 20210413

ACTIVE INGREDIENTS: HYDROXYETHYL CELLULOSE (140 CPS AT 5%) 0.381 g/30 mL
INACTIVE INGREDIENTS: SODIUM BENZOATE 0.3 mL/30 mL; WATER 25.008 mL/30 mL; POLYSORBATE 20 0.075 mL/30 mL; GLYCERIN 2.538 mL/30 mL; PROPYLENE GLYCOL 1.665 mL/30 mL; LACTIC ACID, DL- 0.006 mL/30 mL; EDETATE DISODIUM ANHYDROUS 0.027 mL/30 mL

Water Based Personal Lubricant, Aopar, 30mL

Active ingredient

Hydroxyethyl Cellulose 1.27% w/w

Inactive ingredient

De-lonized Water, Glycerin, Propylene Glycol, Sodium Benzoate, Polysorbate 20, Disodium EDTA, Lactic Acid

Indication for use

Aopar Water-based Personal Lubricant is a supplement for the nature lubrication of penis or vagina, intending to moisturize and enhance the ease and comfort of intimate sexual activity.

This product is compatible with natural rubber latex, polyurethane and polyisoprene condoms.

When using

Virginal / Anal dryness and/or intimate sexual activity.

This product is not a contraceptive and does not contain a spermicide.

Do not use

This product is not a contraceptive or spermicide.

Stop use

If irriation or discomfor occurs, please discontinue to use and consult a physician.

Very slippery surfaces, clean the spills immediately.

Ask doctor

If irriation or discomfor occurs, please discontinue to use and consult a doctor/physician.

Ask doctor/pharmacist

If irriation or discomfor occurs, please discontinue to use and consult a doctor/physician.

Keep out of reach of children

Keep out of children and pets' reach.

Questions

Please contact us when you have any questions.

86-755-83286325 / services@aopar.com

Pregnancy or breast feeding

Pregnant or breast feeding women shall follow doctor advice.

Indications & usage

Aopar Water-based Personal Lubricant is a supplement for the nature lubrication of penis or vagina, intending to moisturize and enhance the ease and comfort of intimate sexual activity.

This product is compatible with natural rubber latex, polyurethane and polyisoprene condoms.

This product is not a contraceptive or spermicide.

Direction

Apply a small amount to genital areas. Reapply as needed or desired.

Dosage forms & strengths

The lubricant is like oil form.

The active ingredient strength is 1.27% w/w.

Warnings

If irriation or discomfor occurs, please discontinue to use and consult a physician.

Very slippery surfaces, clean the spills immediately.

This product is not a contraceptive or spermicide.

Keep out of children and pets' reach.